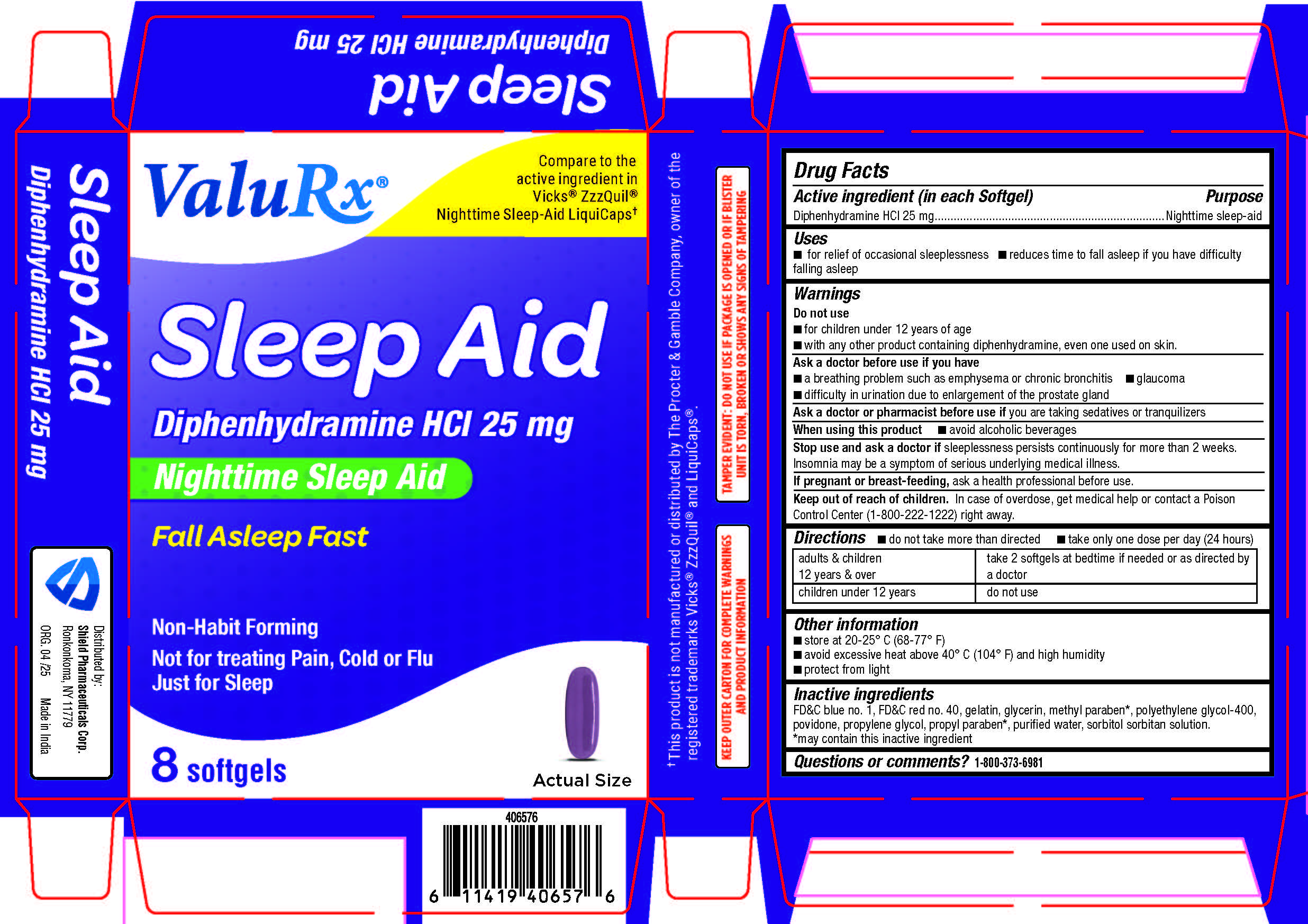 DRUG LABEL: SLEEP AID
NDC: 83059-0115 | Form: CAPSULE, LIQUID FILLED
Manufacturer: Shield Pharmaceuticals Corp
Category: otc | Type: HUMAN OTC DRUG LABEL
Date: 20251112

ACTIVE INGREDIENTS: DIPHENHYDRAMINE HYDROCHLORIDE 25 mg/1 1
INACTIVE INGREDIENTS: FD&C BLUE NO. 1; FD&C RED NO. 40; GELATIN; GLYCERIN; METHYLPARABEN; POLYETHYLENE GLYCOL 400; PROPYLENE GLYCOL; POVIDONE; PROPYLPARABEN; SORBITOL SOLUTION; SORBITAN; WATER

SLEEP-AID

Drug Facts

Active ingredients (in each softgel)

Diphenhydramine HCl 25 mg

Purpose

nighttime sleep-aid

Uses

- for the relief of occasional sleeplessness
- reduces time to fall asleep if you have difficulty falling asleep

Warnings

Do not use

- for children under 12 years of age
- with any other product containing diphenhydramine, even one used on skin.

Ask a doctor before use if you have

- a breathing problem such as asthma, emphysema, or chronic bronchitis
- glaucoma
- difficulty in urination due to enlargement of the prostate gland
- heart disease

Ask a doctor or pharmacist before use if you aretaking sedatives, tranquilizers or any other sleep aid

When using this product

- avoid alcoholic beverages and other drugs that cause drowsiness
- drowsiness will occur
- be careful when driving a motor vehicle or operating machinery

Stop use and ask a doctor ifsleeplessness persists continuously for more than 2 weeks. Insomnia may be a symptom of serious underlying medical illness.

PREGNANCY OR BREAST FEEDING

If pregnant or breast-feeding,ask a health professional before use.

Keep out of reach of children.Overdose warning: Taking more than directed can cause serious health problems. In case of overdose, get medical help or contact a Poison Control Center right away. 1(800)222-1222

Directions

- do not take more than directed
- take only one dose per day (24 hours)

adults & children 12 yrs & over | take 2 capsules at bedtime if needed or as directed by a doctor
children under 12 years | Do not use

Other information

- store at 20-25°C (68-77°F)
- avoid excessive heat above 40°C (104°F) and high humidity
- Protect from light

Inactive ingredients

FD&C blue no. 1, FD&C red no. 40, gelatin, glycerin, methylparaben*, polyethylene glycol-400, povidone, propylene glycol, propylparaben*, purified water, sorbitol sorbitan solution. *may contain this inactive ingredient

Questions or comments?

1-800-373-6981

QUESTIONS

Distributed by:
Shield Pharmaceuticals Corp.
Ronkonkoma, NY 11779

PACKAGE LABEL

Sleep Aid

Diphenhydramine HCl 25 mg

Fall Asleep Fast

- Non-Habit Forming
- Not for treating Pain, Cold or Flu
- Just for Sleep

Carton